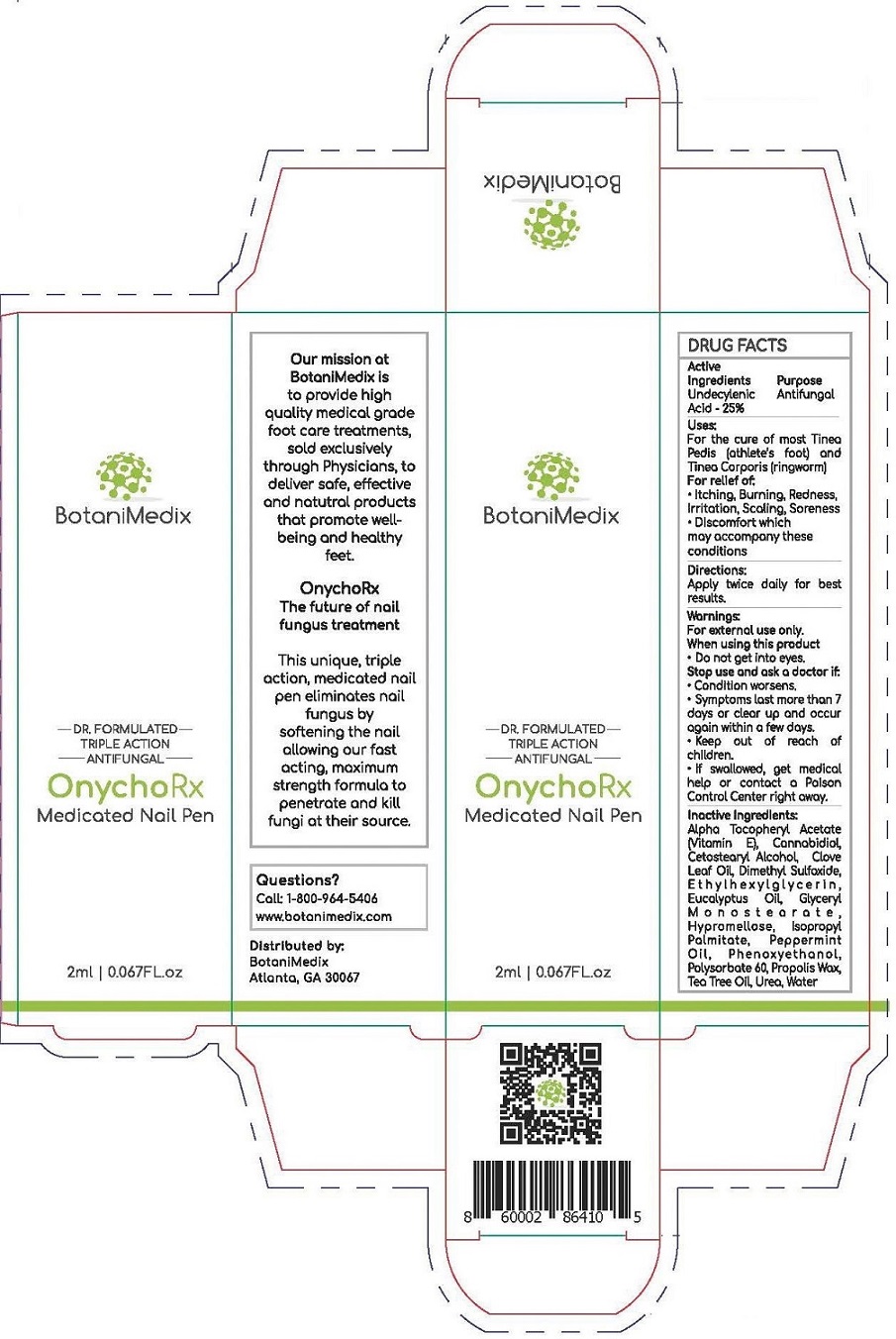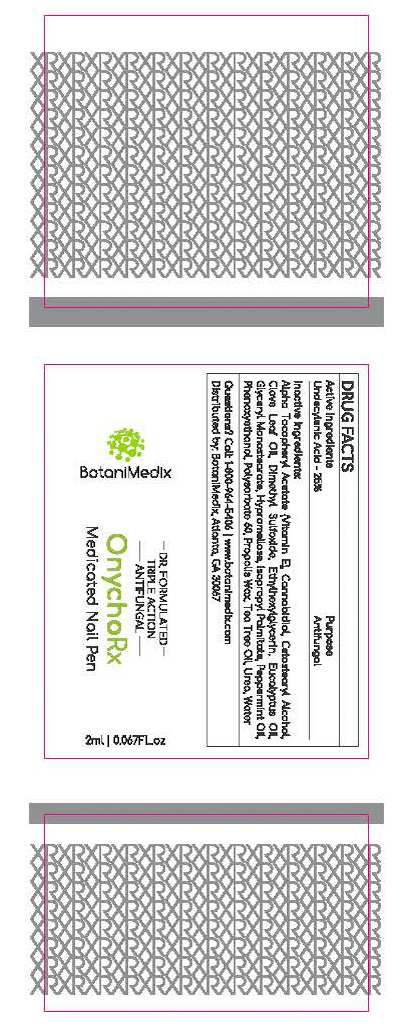 DRUG LABEL: Botanimedix OnychoRX Antifungal Nail Gel
NDC: 52261-5800 | Form: GEL
Manufacturer: Cosco International, Inc.
Category: otc | Type: HUMAN OTC DRUG LABEL
Date: 20200129

ACTIVE INGREDIENTS: UNDECYLENIC ACID 0.2508 kg/1 kg
INACTIVE INGREDIENTS: ISOPROPYL PALMITATE; CETOSTEARYL ALCOHOL; POLYSORBATE 60; GLYCERYL MONOSTEARATE; UREA; PEPPERMINT OIL; .ALPHA.-TOCOPHEROL ACETATE, DL-; PROPOLIS WAX; HYPROMELLOSE 2208 (15000 MPA.S); WATER; TEA TREE OIL; EUCALYPTUS OIL; PHENOXYETHANOL; ETHYLHEXYLGLYCERIN; CANNABIDIOL; CLOVE LEAF OIL; DIMETHYL SULFOXIDE

Botanimedix OnychoRX Antifungal Nail Gel

DRUG FACTS

Active Ingredient Purpose
Undecylenic Acid 25%........................Anti-fungal

Uses:

For the cure of most Tinea Pedis (athlete's foot) and Tinea Corporis (ringworm)

INDICATIONS AND USAGE

For relief of:

Itching, Burning, Redness, Irratation, Scaling, Soreness
Discomfort which may accompany these conditions

Directions:

Apply twice daily for best results.

Warnings:

For external use only.

When using this product

- Do not get into eyes.

Stop use and ask a doctor if:

- Condition worsens.
- Symptoms last more than 7 days or clear and occur again within a few days.

Keep out of reach of children.

- If swallowed, get medical help or contact a Poison Control Center right away.

Inactive Ingredients:

Alpha Tocopheryl Acetate (Vitamin E), Cannabidiol, Cetostearyl Alchohol, Clove Leaf Oil, Dimethyl Sulfoxide, Ethylhexylglycerin, Eucalyptus Oil, Glyceryl Monostearate, Hypromellose, Isopropyl Palmitate, Peppermint Oil, Phenoxyethanol, Polysorbate 60, Propolis Wax, Tea Tree Oil, Urea, Water

Questions?

Call: 1-800-964-5406

www.botanimedix.com

Distributed by:

BotaniMedix

Atlanta, GA 30067